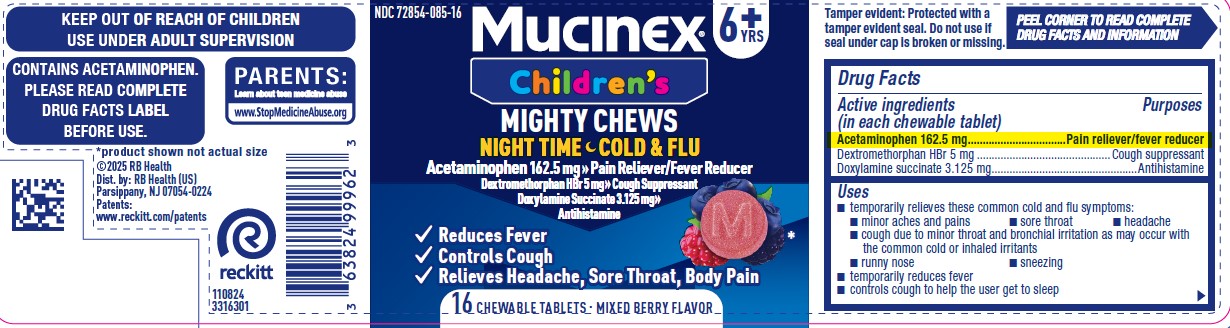 DRUG LABEL: Mucinex Childrens Mighty Chews Night Time Cold and Flu
NDC: 72854-085 | Form: TABLET, CHEWABLE
Manufacturer: RB Health (US) LLC
Category: otc | Type: HUMAN OTC DRUG LABEL
Date: 20251126

ACTIVE INGREDIENTS: DEXTROMETHORPHAN HYDROBROMIDE 5 mg/1 1; DOXYLAMINE SUCCINATE 3.125 mg/1 1; ACETAMINOPHEN 162.5 mg/1 1
INACTIVE INGREDIENTS: MALIC ACID; CORN SYRUP; FD&C BLUE NO. 1; SODIUM CHLORIDE; ANHYDROUS TRISODIUM CITRATE; SUCRALOSE; SODIUM POLYMETAPHOSPHATE; SUCROSE; ANHYDROUS CITRIC ACID; ETHYLCELLULOSE; FD&C RED NO. 40; MALTODEXTRIN; PECTIN; POTASSIUM SODIUM TARTRATE; WATER; GLYCERIN

Mucinex Children's Mighty Chews Cough Nighttime

ACTIVE INGREDIENT

Acetaminophen 162.5 mg

Dextromethorphan HBr 5 mg

Doxylamine succinate 3.125 mg

PURPOSE

Acetaminophen 162.5 mg................................................Pain reliever/fever reducer

Dextromethorphan HBr 5 mg.......................... ...............Cough suppressant
Doxylamine succinate 3.125 mg.................................................Antihistamine

Uses

■ temporarily relieves these common cold and flu symptoms:

■ minor aches and pains

■ sore throat

■ headache
■ cough due to minor throat and bronchial irritation as may occur with
the common cold or inhaled irritants
■ runny nose

■ sneezing
■ temporarily reduces fever
■ controls cough to help the user get to sleep

Warnings

Liver warning: This product contains acetaminophen. Severe liver damage
may occur if:
■ adult takes more than 6 doses (24 chewable tablets) in 24 hours, which is
the maximum daily amount
■ child takes more than 5 doses (10 chewable tablets) in 24 hours, which is
the maximum daily amount
■ taken with other drugs containing acetaminophen
■ adult has 3 or more alcoholic drinks every day while using this product

Allergy alert: Acetaminophen may cause severe skin reactions.
Symptoms may include:
■ skin reddening ■ blisters ■ rash

If a skin reaction occurs, stop use and seek medical help right away.
Sore throat warning: If sore throat is severe, persists for more than 2 days,
is accompanied or followed by fever, headache, rash, nausea, or vomiting,
consult a doctor promptly.

Do not use
■ to make a child sleepy
■ with any other drug containing acetaminophen (prescription or
nonprescription). If you are not sure whether a drug contains
acetaminophen, ask a doctor or pharmacist.
■ if the user is now taking a prescription monoamine oxidase inhibitor
(MAOI) (certain drugs for depression, psychiatric, or emotional conditions,
or Parkinson’s disease), or for 2 weeks after stopping the MAOI drug. If
you do not know if your prescription drug contains an MAOI, ask a doctor
or pharmacist before taking this product.

Ask a doctor before use if you have
■ has liver disease
■ has a sodium-restricted diet
■ has glaucoma
■ has a breathing problem such as emphysema or chronic bronchitis
■ has difficulty in urination due to enlargement of the prostate gland
■ is a child with pain of arthritis

Ask a doctor or pharmacist before use if you are
■ taking the blood thinning drug warfarin
■ taking sedatives or tranquilizers

When using this product
■ do not use more than directed (see Overdose warning)
■ excitability may occur, especially in children
■ marked drowsiness may occur
■ alcohol, sedatives, and tranquilizers may increase the drowsiness effect
■ avoid alcoholic beverages
■ use caution when driving a motor vehicle or operating machinery

Stop use and ask a doctor if
■ pain or cough gets worse or lasts more than 5 days (children) or 7 days (adults)
■ fever gets worse or lasts more than 3 days
■ redness or swelling is present
■ new symptoms occur
■ cough comes back or occurs with rash or headache that lasts. These could be
signs of a serious condition.

KEEP OUT OF REACH OF CHILDREN

If pregnant or breast-feeding, ask a health professional before use.

Keep out of reach of children.

Overdose warning: Taking more than the recommended dose (overdose) may
cause liver damage. In case of overdose, get medical help or contact a Poison
Control Center right away. Prompt medical attention is critical for adults as
well as for children even if you do not notice any signs or symptoms.

Directions
■ do not take more than directed (see Overdose warning)
■ chew thoroughly before swallowing
■ dose every 4 hours or as directed by a doctor

adults and children 12 years of age and over | 4 chewable tablets every 4 hours, not to exceed 6 doses (24 chewable tablets) in any 24-hour period
children 6 to under 12 years of age | 2 chewable tablets every 4 hours, not to exceed 5 doses (10 chewable tablets) in any 24-hour period
children under 6 years of age | do not use

Other information
■ each chewable tablet contains: potassium 5 mg and sodium 13 mg
■ Store in a cool dry place at 20-25°C (68-77°F)

Inactive ingredients

anhydrous citric acid, corn syrup, ethylcellulose, FD&C blue no. 1, FD&C red no. 40,
flavor, glycerin, malic acid, maltodextrin, pectin, potassium sodium tartrate,
purified water, sodium chloride, sodium polymetaphosphate, sucralose,
sucrose, trisodium citrate (anhydrous)

Questions? 1-866-MUCINEX (1-866-682-4639)

PACKAGE LABEL

NDC 72854-085-16

Children's
Mucinex®

Cough Suppressant

Antihistamine

Acetaminophen 162.5 mg

Dextromethorphan HBr 5 mg

Doxylamine succinate 3.125 m

Age 6+

Mixed Berry Flavor